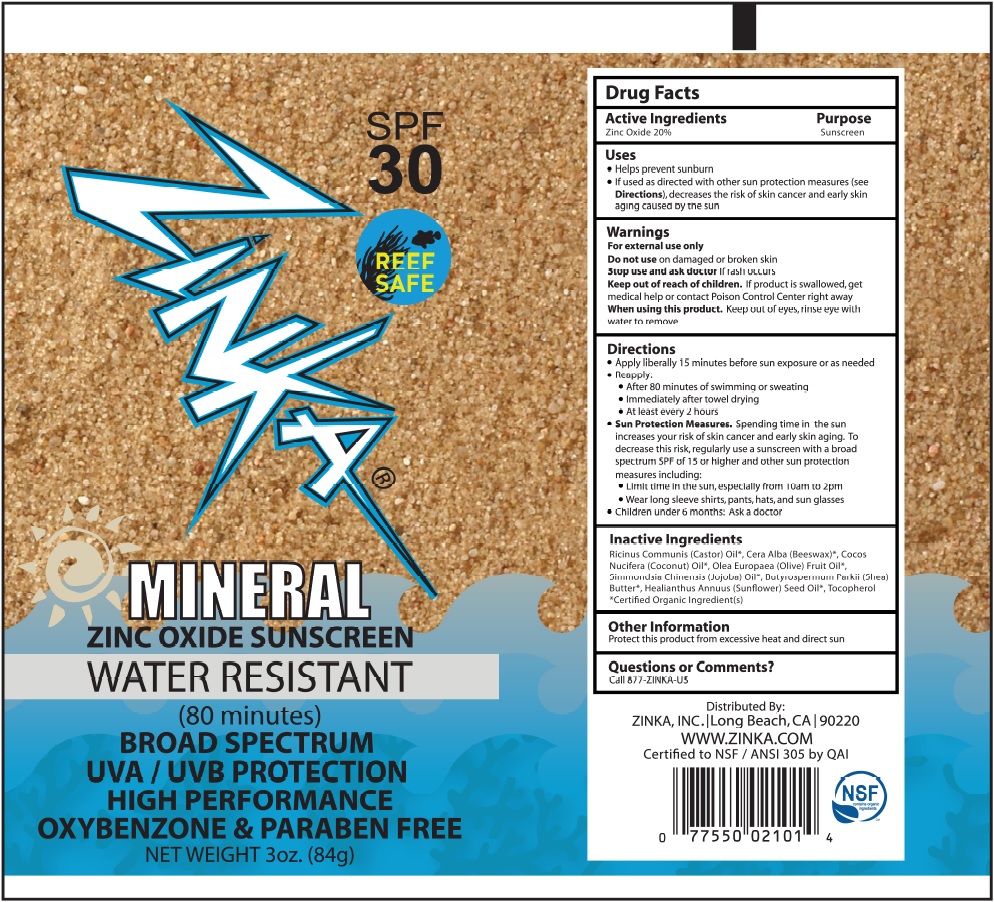 DRUG LABEL: SUNSCREEN
NDC: 62932-190 | Form: OINTMENT
Manufacturer: Private Label Select Ltd CO
Category: otc | Type: HUMAN OTC DRUG LABEL
Date: 20181130

ACTIVE INGREDIENTS: ZINC OXIDE 20 g/100 g
INACTIVE INGREDIENTS: CASTOR OIL; SIMMONDSIA CHINENSIS SEED WAX; TOCOPHEROL; COCONUT OIL; OLEA EUROPAEA FRUIT VOLATILE OIL; SHEA BUTTER; YELLOW WAX; HELIANTHUS ANNUUS SEED WAX

Zinka Sunscreen SPF30